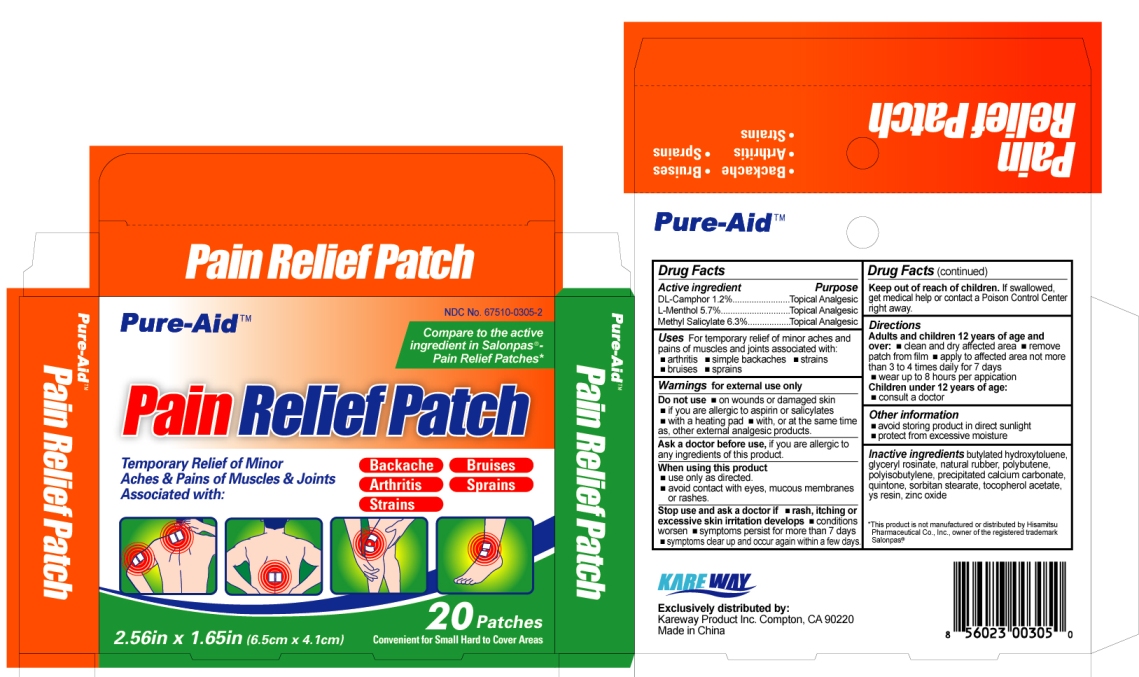 DRUG LABEL: Pain Relief
NDC: 67510-0305 | Form: PATCH
Manufacturer: Kareway Product, Inc.
Category: otc | Type: HUMAN OTC DRUG LABEL
Date: 20171205

ACTIVE INGREDIENTS: CAMPHOR (SYNTHETIC) 0.4 mg/1 1; LEVOMENTHOL 1.8 mg/1 1; METHYL SALICYLATE 2 mg/1 1
INACTIVE INGREDIENTS: BUTYLATED HYDROXYTOLUENE; NATURAL LATEX RUBBER; CALCIUM CARBONATE; SORBITAN MONOSTEARATE; ALPHA-TOCOPHEROL ACETATE; ZINC OXIDE

Drug Facts

Active ingredient

DL-Camphor 1.2%

L-Menthol 5.7%

Methyl Salicylate 6.3%

Purpose

Topical Analgesic

Topical Analgesic

Topical Analgesic

Uses

For temporary relief of minor aches and pains of muscles and joints associated with:

- arthritis
- simple backaches
- strains
- bruises
- sprains

Warnings

for external use only

Do not use

- on wounds or damaged skin
- if you are allergic to aspirin or salicylates
- with a heating pad
- with, or at the same time as, other external analgesic products

Ask a doctor before use,

if you are allergic to any ingredients of this product.

When using this product

- use only as directed
- avoid contact with eyes, mucous membranes or rashes

Stop use and ask a doctor if

- rash, itching or excessive skin irritation develops
- conditions worsen
- symptoms persist for more than 7 days
- symptoms clear up and occur again within a few days

Keep out of reach of children.

If swallowed, get medical help or contact a Poison Control Center right away.

Directions

Adults and children 12 years of age and over:

- clean and dry affected area
- remove patch from film
- apply to affected area not more than 3 to 4 times daily for 7 days
- wear up to 8 hours per application

Children under 12 years of age:

- consult a doctor

Other information

- avoid storing product in direct sunlight
- protect from excessive moisture

Inactive ingredients

butylated hydroxytoluene, glyceryl rosinate, natural rubber, polybutene, polyisobutylene, precipitated calcium carbonate, quintone, sorbitan stearate, tocopherol acetate, ys resin, zinc oxide

Carton label

Pain Relief Patch